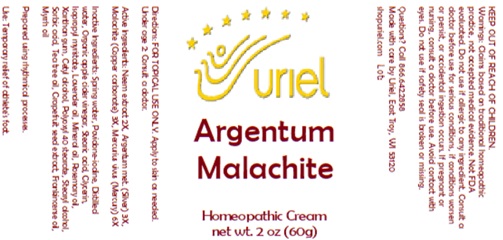 DRUG LABEL: Argentum Malachite
NDC: 48951-1309 | Form: CREAM
Manufacturer: Uriel Pharmacy Inc.
Category: homeopathic | Type: HUMAN OTC DRUG LABEL
Date: 20250627

ACTIVE INGREDIENTS: CUPRIC CATION 3 [hp_X]/1 g; MERCURY 6 [hp_X]/1 g; SILVER 3 [hp_X]/1 g; AZADIRACHTA INDICA FLOWER 2 [hp_X]/1 g
INACTIVE INGREDIENTS: LAVENDER OIL; MINERAL OIL; WATER; STEARIC ACID; ISOPROPYL MYRISTATE; POVIDONE-IODINE; ROSEMARY OIL; CETYL ALCOHOL; STEARYL ALCOHOL; SORBIC ACID; TEA TREE OIL; POLYOXYL 40 STEARATE; XANTHAN GUM; FRANKINCENSE OIL; MYRRH OIL; CITRUS PARADISI SEED; ACETIC ACID; GLYCERIN

Argentum Malachite

INDICATIONS AND USAGE

Directions: FOR TOPICAL USE ONLY.

DOSAGE AND ADMINISTRATION

Apply to skin as needed. Under age 2: Consult a doctor.

ACTIVE INGREDIENT

Active Ingredients: Neem extract 2X, Argentum met. (Silver) 3X, Malachite (Copper carbonate) 3X, Mercurius vivus (Mercury) 6X

INACTIVE INGREDIENT

Inactive Ingredients: Spring water, Organic vinegar, Stearic acid, Glycerin, Isopropyl myristate, Lavender oil, Mineral oil, Povidone-iodine, Rosemary oil, Cetyl alcohol, Polyoxyl 40 stearate, Stearyl alcohol, Xanthan gum, Sorbic acid, Tea tree oil, Frankincense oil, Myrrh oil, Grapefruit seed extract

Prepared using rhythmical processes.

PURPOSE

Use: Temporary relief of athlete's foot.

KEEP OUT OF REACH OF CHILDREN.

WARNINGS

Warnings: Claims based on traditional homeopathic practice, not accepted medical evidence. Not FDA evaluated. Do not use if allergic to any ingredient. Consult a doctor before use for serious conditions, if conditions worsen or persist, or accidental ingestion occurs. If pregnant or nursing, consult a doctor before use. Avoid contact with eyes. Do not use if safety seal is broken or missing.

Questions? Call 866.642.2858
Made with care by Uriel, East Troy, WI 53120
shopuriel.com Lot: